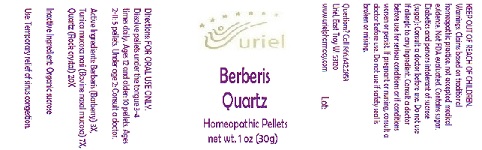 DRUG LABEL: BERBERIS QUARTZ
NDC: 48951-2055 | Form: PELLET
Manufacturer: URIEL PHARMACY INC.
Category: homeopathic | Type: HUMAN OTC DRUG LABEL
Date: 20180601

ACTIVE INGREDIENTS: BERBERIS VULGARIS ROOT BARK 3 [hp_X]/1 1; BOS TAURUS NASAL MUCOSA 7 [hp_X]/1 1; SILICON DIOXIDE 20 [hp_X]/1 1
INACTIVE INGREDIENTS: SUCROSE

Berberis Quartz

INDICATIONS AND USAGE

Directions: FOR ORAL USE ONLY.

DOSAGE AND ADMINISTRATION

Dissolve pellets under the tongue 3-4
times daily. Ages 12 and older: 10 pellets.
Ages 2-11: 5 pellets. Under age 2: Consult
a doctor.

ACTIVE INGREDIENT

Active Ingredients: Berberis (Barberry) 3X, Tunica mucosa nasi (Bovine nasal mucosa) 7X, Quartz (Rock crystal) 20X

Inactive Ingredient: Sucrose

PURPOSE

Use: Temporary relief of sinus congestion.

KEEP OUT OF REACH OF CHILDREN.

WARNINGS

Warnings: Claims based on traditional homeopathic practice, not accepted medical evidence. Not FDA evaluated. Contains sugar. Diabetics and persons intolerant of sucrose (sugar): Consult a doctor before use. Do not use if allergic to any ingredient. Consult a doctor before use for serious conditions or if conditions worsen or persist. If pregnant or nursing, consult a doctor before use. Do not use if safety seal is broken or missing.

Questions? Call 866.642.2858
Uriel, East Troy WI 53120